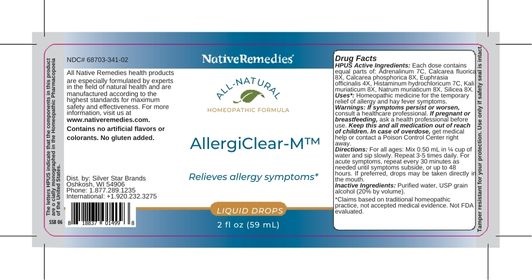 DRUG LABEL: AllergiClear-M
NDC: 68703-341 | Form: LIQUID
Manufacturer: Silver Star Brands
Category: homeopathic | Type: HUMAN OTC DRUG LABEL
Date: 20250101

ACTIVE INGREDIENTS: CALCIUM PHOSPHATE 8 [hp_X]/59 mL; CALCIUM FLUORIDE 8 [hp_X]/59 mL; EUPHRASIA OFFICINALIS LEAF 4 [hp_X]/59 mL; EPINEPHRINE 7 [hp_C]/59 mL; HISTAMINE DIHYDROCHLORIDE 7 [hp_C]/59 mL; SILICON DIOXIDE 8 [hp_X]/59 mL; SODIUM CHLORIDE 8 [hp_X]/59 mL; POTASSIUM CHLORIDE 8 [hp_X]/59 mL
INACTIVE INGREDIENTS: WATER; ALCOHOL

NativeRemedies® AllergiClear-M™

HPUS Active Ingredient

HPUS Active Ingredients: Each dose contains equal parts of: Adrenalinum 7C, Calcarea fluorica 8X, Calcarea phosphorica 8X, Euphrasia officinalis 4X, Histaminum hydrochloricum 7C, Kali muriaticum 8X, Natrum muriaticum 8X, Silicea 8X.

The letters HPUS indicate that the components in this product are officially monographed in the Homeopathic Pharmacopoeia of the United States.

Uses*

Uses*: Homeopathic medicine for the temporary relief of allergy and hay fever symptoms.

*Claims based on traditional homeopathic practice, not accepted medical evidence. Not FDA evaluated.

Warnings

Warnings: If symptoms persist or worsen, consult a healthcare professional. If pregnant or breastfeeding, ask a healthcare professional before use. Keep this and all medication out of reach of children. In case of overdose, get medical help or contact a Poison Control Center right away.

Directions

Directions: For all ages: Mix 0.50 mL in 1/4 cup of water and silp slowly. Repeat 3-5 times daily. For acute symptoms, repeat every 30 minutes as needed until symptoms subside, or up to 48 hours. If preferred, drops may be taken directly in the mouth.

OTHER SAFETY INFORMATION

Contains no artificial flavors or colorants. No gluten added.

Tamper resistant for your protection. Use only if safety seal is intact.

Inactive Ingredients

Inactive Ingredients: Purified water, USP grain alcohol (20% by volume).

KEEP OUT OF REACH OF CHILDREN

Keep this and all medication out of reach of children.

PREGNANCY OR BREAST FEEDING

If pregnant or breastfeeding, ask a health professional before use.

PURPOSE

Relieves allergy symptoms